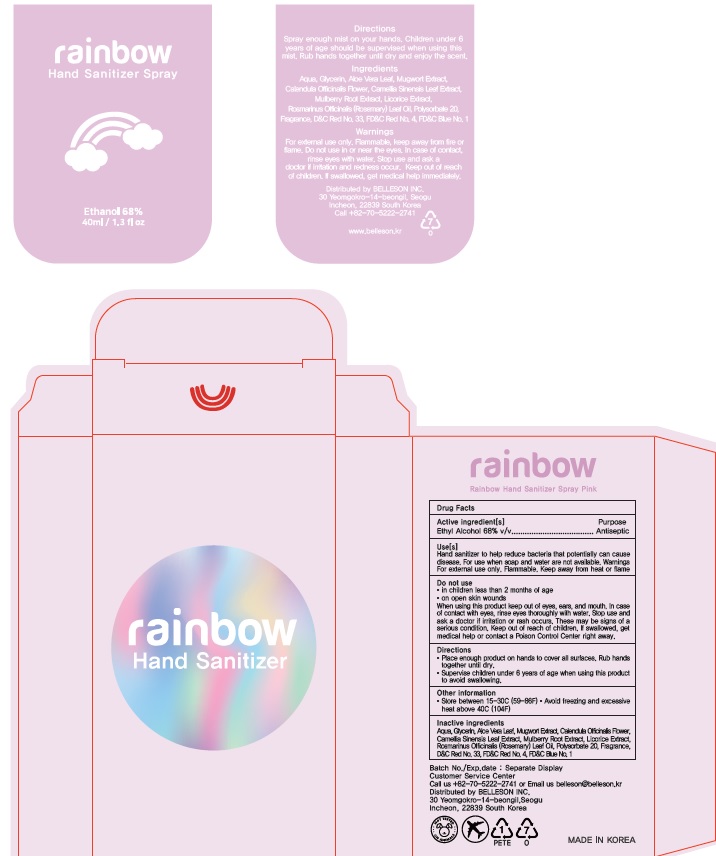 DRUG LABEL: Rainbow Hand Sanitizer Pink
NDC: 75063-0007 | Form: LIQUID
Manufacturer: Belleson Inc
Category: otc | Type: HUMAN OTC DRUG LABEL
Date: 20211001

ACTIVE INGREDIENTS: ALCOHOL 68 mL/100 mL
INACTIVE INGREDIENTS: WATER; GLYCERIN; ALOE VERA LEAF; ARTEMISIA PRINCEPS LEAF; CALENDULA OFFICINALIS FLOWER; MORUS ALBA ROOT; LICORICE; ROSEMARY OIL; POLYSORBATE 20; D&C RED NO. 33; FD&C RED NO. 4; FD&C BLUE NO. 1; GREEN TEA LEAF

Active ingredient

Ethyl Alcohol 68% v/v

Purpose

Antiseptic

Uses

Hand sanitizer to help reduce bacteria that potentially can cause
disease. For use when soap and water are not available.

Warnings For external use only. Flammable. Keep away from heat or flame

Warnings

Do not use
• in children less than 2 months of age
• on open skin wounds
When using this product keep out of eyes, ears, and mouth. In case of contact with eyes, rinse eyes thoroughly with water.

Stop use and ask a doctor if irritation or rash occurs. These may be signs of a serious condition.

Keep out of reach of children. If swallowed, get medical help or contact a Poison Control Center right away.

Directions

• Place enough product on hands to cover all surfaces. Rub hands together until dry.
• Supervise children under 6 years of age when using this product to avoid swallowing.

Other information

Store between 15-30C (59-86F) • Avoid freezing and excessive
heat above 40C (104F)

Inactive ingredients

Aqua, Glycerin, Aloe Vera Leaf, Mugwort Extract, Calendula Officinalis Flower,Camellia Sinensis Leaf Extract, Mulberry Root Extract, Licorice Extract,Rosmarinus Officinalis (Rosemary) Leaf Oil, Polysorbate 20, Fragrance,D&C Red No. 33, FD&C Red No. 4, FD&C Blue No. 1